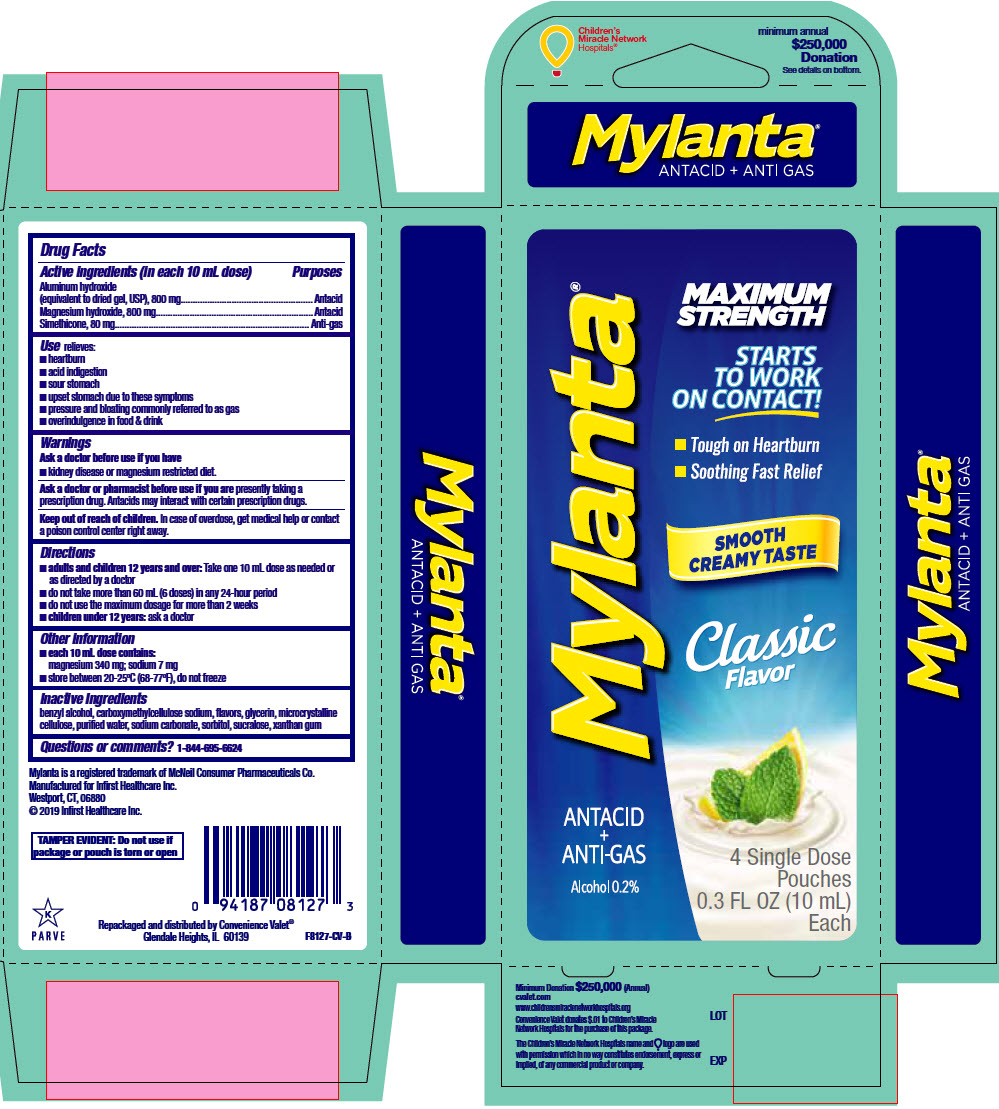 DRUG LABEL: MYLANTA MAXIMUM STRENGTH CLASSIC FLAVOR antacid and anti gas
NDC: 29485-8127 | Form: LIQUID
Manufacturer: Lil' Drug Store Products, Inc.
Category: otc | Type: HUMAN OTC DRUG LABEL
Date: 20230719

ACTIVE INGREDIENTS: ALUMINUM HYDROXIDE 800 mg/10 mL; MAGNESIUM HYDROXIDE 800 mg/10 mL; DIMETHICONE 80 mg/10 mL
INACTIVE INGREDIENTS: BENZYL ALCOHOL; CARBOXYMETHYLCELLULOSE SODIUM, UNSPECIFIED FORM; GLYCERIN; MICROCRYSTALLINE CELLULOSE; WATER; SODIUM CARBONATE; SORBITOL; SUCRALOSE; XANTHAN GUM

MYLANTA® MAXIMUM STRENGTH CLASSIC FLAVOR antacid and anti gas aluminum hydroxide magnesium hydroxide and simethicone suspension

Drug Facts

ACTIVE INGREDIENT

PURPOSE

Active ingredients (in each 10 mL dose) | Purposes
Aluminum hydroxide (equivalent to dried gel, USP), 800 mg | Antacid
Magnesium hydroxide, 800 mg | Antacid
Simethicone, 80 mg | Anti-gas

Use

relieves:

- heartburn
- acid indigestion
- sour stomach
- upset stomach due to these symptoms
- pressure and bloating commonly referred to as gas
- overindulgence in food & drink

Warnings

Ask a doctor before use if you have

- kidney disease or magnesium restricted diet.

Ask a doctor or pharmacist before use if you are presently taking a prescription drug. Antacids may interact with certain prescription drugs.

Keep out of reach of children. In case of overdose, get medical help or contact a poison control center right away.

Directions

- adults and children 12 years and over: Take one 10 mL dose as needed or as directed by a doctor
- do not take more than 60 mL (6 doses) in any 24-hour period
- do not use the maximum dosage for more than 2 weeks
- children under 12 years: ask a doctor

Other information

- each 10 mL dose contains:
  magnesium 340 mg; sodium 7 mg
- store between 20-25°C (68-77°F), do not freeze

Inactive Ingredients

benzyl alcohol, carboxymethylcellulose sodium, flavors, glycerin, microcrystalline cellulose, purified water, sodium carbonate, sorbitol, sucralose, xanthan gum

Questions or comments?

1-844-695-6624

Repackaged and distributed by Convenience Valet®
Glendale Heights, IL 60139

PRINCIPAL DISPLAY PANEL - 10 mL Pouch Carton

Mylanta®

MAXIMUM
STRENGTH

STARTS
TO WORK
ON CONTACT!

- Tough on Heartburn
- Soothing Fast Relief

SMOOTH
CREAMY TASTE

Classic
Flavor

ANTACID
+
ANTI-GAS

Alcohol 0.2%

4 Single Dose
Pouches
0.3 FL OZ (10 mL)
Each